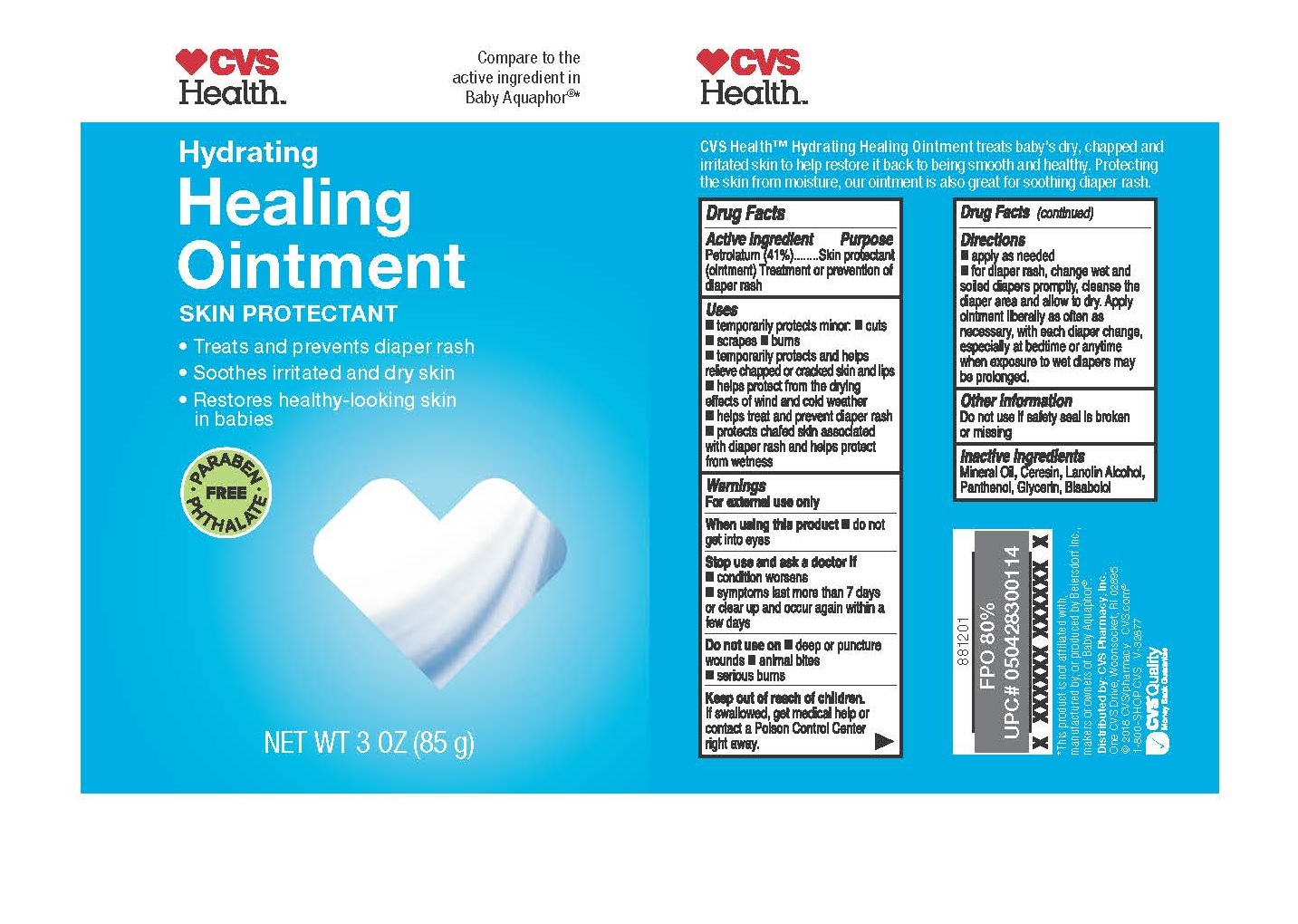 DRUG LABEL: Hydrating Healing Skin Protectant
NDC: 59779-853 | Form: OINTMENT
Manufacturer: CVS Pharmacy
Category: otc | Type: HUMAN OTC DRUG LABEL
Date: 20260114

ACTIVE INGREDIENTS: PETROLATUM 41 g/100 g
INACTIVE INGREDIENTS: MINERAL OIL; CERESIN; LANOLIN ALCOHOLS; PANTHENOL; GLYCERIN; .ALPHA.-BISABOLOL, (+/-)-

CVS Hydrating Healing Ointment 3oz

Active Ingredient

Petrolatum 41%

Purpose

Skin protectant (ointment) Treatment or prevention of diaper rash

Uses

temporarily protects minor: cuts, scrapes, burns

temporarily protects and helps relieve chapped or cracked skin and lips

helps protect from the drying effects of wind and cold weather

helps treat and prevent diaper rash

protects chafed skin associated with diaper rash and helps protect from wetness

Warnings

For external use only

When using this product

do not get into eyes

Stop use and ask a doctor if

condition worsens, symptoms last more than 7 days or clear up and occur again within a few days.

Do not use on

deep or puncture wounds, animal bites, serious burns

Keep out of reach of children

If swallowed, get medical help or contact a Poison Control Center right away.

Directions

apply as needed

for diaper rash, change wet and soiled diapers promptly, cleanse the diaper area and allow to dry. Apply ointment liberally as often as necessary, with each diaper change, especially at bedtime or anytime when exposure to wet diapers may be prolonged.

Other information

Do not use if safety seal is broken or missing

Inactive ingredients

Mineral Oil, Ceresin, Lanolin Alcohol, Panthenol, Glycerin, Bisabolol